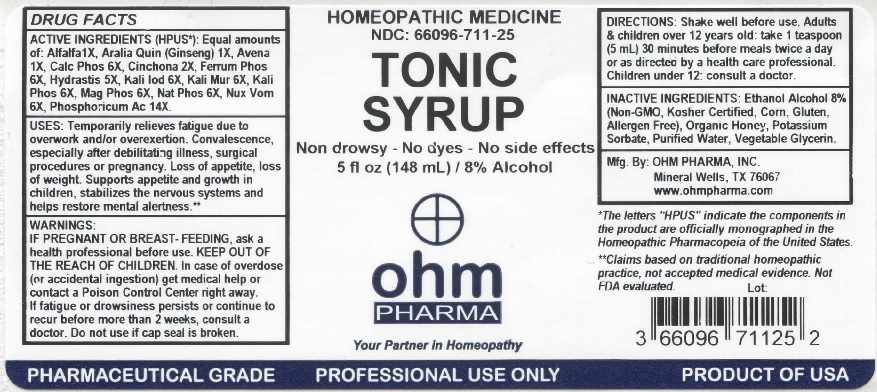 DRUG LABEL: OHM Tonic Syrup
NDC: 66096-711 | Form: LIQUID
Manufacturer: OHM PHARMA INC.
Category: homeopathic | Type: HUMAN PRESCRIPTION DRUG LABEL
Date: 20211229

ACTIVE INGREDIENTS: ALFALFA 1 [hp_X]/148 mL; AMERICAN GINSENG 1 [hp_X]/148 mL; AVENA SATIVA FLOWERING TOP 1 [hp_X]/148 mL; TRIBASIC CALCIUM PHOSPHATE 6 [hp_X]/148 mL; CINCHONA BARK 2 [hp_X]/148 mL; FERROSOFERRIC PHOSPHATE 6 [hp_X]/148 mL; GOLDENSEAL 5 [hp_X]/148 mL; POTASSIUM IODIDE 6 [hp_X]/148 mL; POTASSIUM CHLORIDE 6 [hp_X]/148 mL; DIBASIC POTASSIUM PHOSPHATE 6 [hp_X]/148 mL; MAGNESIUM PHOSPHATE, DIBASIC TRIHYDRATE 6 [hp_X]/148 mL; SODIUM PHOSPHATE, DIBASIC, HEPTAHYDRATE 6 [hp_X]/148 mL; STRYCHNOS NUX-VOMICA SEED 6 [hp_X]/148 mL; PHOSPHORIC ACID 14 [hp_X]/148 mL
INACTIVE INGREDIENTS: ALCOHOL; HONEY; POTASSIUM SORBATE; WATER; GLYCERIN

OHM Tonic Syrup

ACTIVE INGREDIENT

ACTIVE INGREDIENTS (HPUS*): Equal amounts of: Alfalfa 1X, Aralia Quin (Ginseng) 1X, Avena 1X, Calc Phos 6X, Cinchona 2X, Ferrum Phos 6X, Hydrastis 5X, Kali Iod 6X, Kali Mur 6X, Kali Phos 6X, Mag Phos 6X, Nat Phos 6X, Nux Vom 6X, Phosphoricum Ac 14X.

*The letters "HPUS" indicate that the components in this product are officially monographed in the Homeopathic Pharmacopeia of the United States.

INDICATIONS AND USAGE

USES: Temporarily relieves fatigue due to overwork and/or overexertion. Convalescence, especially after debilitating illness, surgical procedures or pregnancy. Loss of appetite, loss of weight. Supports appetite and growth in children, stabilizes the nervous systems and helps restore mental alertness.**

**Claims based on traditional homeopathic practice, not accepted medical evidence. Not FDA evaluated.

WARNINGS

WARNINGS: IF PREGNANT OR BREAST-FEEDING, ask a health professional before use. In case over overdose (or accidental ingestion) get medical help or contact a Poison Control Center right away. If fatigue or drowsiness persists or continue to recur before more than 2 weeks, consult a doctor.

- KEEP OUT OF REACH OF CHILDREN.

DOSAGE AND ADMINISTRATION

DIRECTIONS: Shake well before use. Adults & children over 12 years old: take 1 teaspoon (5 mL) 30 minutes before meals twice a day or as directed by a health care professional. Children under 12: consult a doctor.

Do not use if cap seal is broken.

INACTIVE INGREDIENT

INACTIVE INGREDIENTS: Ethanol Alcohol 8% (Non-GMO, Kosher Certified, Corn, Gluten, Allergen Free), Organic Honey, Potassium Sorbate, Purified Water, Vegetable Glycerin.

QUESTIONS

Mfg. By: OHM PHARMA, INC. Mineral Wells, TX 76067

www.ohmpharma.com

PACKAGE LABEL

HOMEOPATHIC MEDICINE

NDC:66096-711-25

TONIC SYRUP

Non Drowsy - No dyes - No side effects

5 fl oz (148 mL) / 8% Alcohol

PRODUCT OF USA

PURPOSE

Relieves fatigue